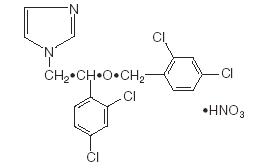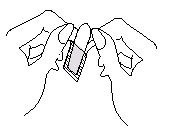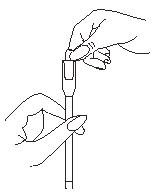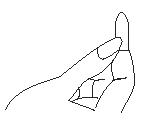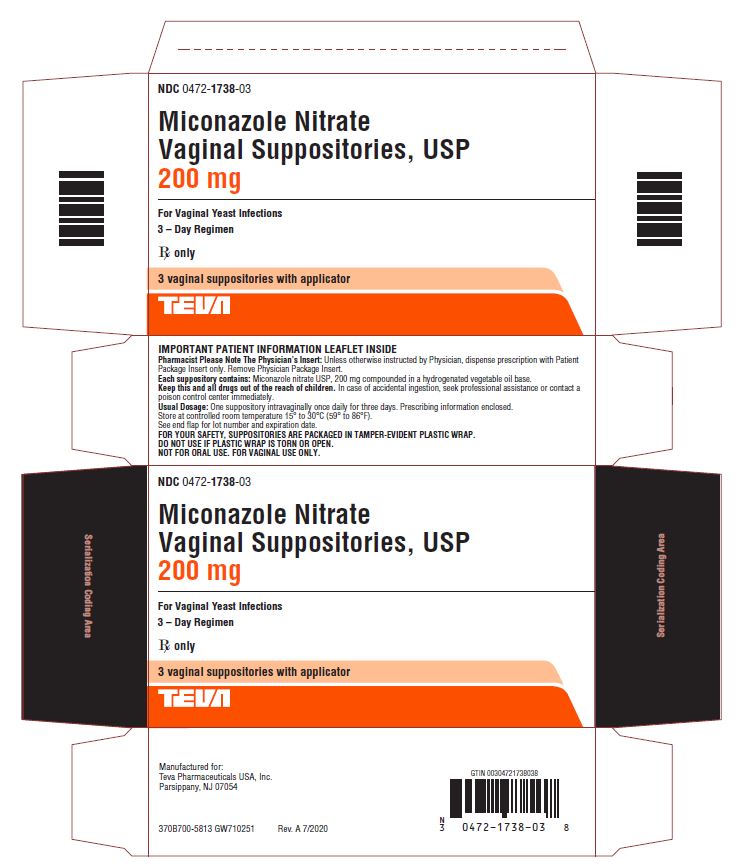 DRUG LABEL: Miconazole Nitrate
NDC: 0472-1738 | Form: SUPPOSITORY
Manufacturer: Actavis Pharma, Inc.
Category: prescription | Type: HUMAN PRESCRIPTION DRUG LABEL
Date: 20201021

ACTIVE INGREDIENTS: MICONAZOLE NITRATE 200 mg/1 1
INACTIVE INGREDIENTS: HYDROGENATED PALM KERNEL OIL

Miconazole Nitrate Vaginal Suppositories USP, 200 mg
PHYSICIAN’S INSERT
Rx only

DESCRIPTION

Miconazole Nitrate Vaginal Suppositories USP, 200 mg are white to off-white suppositories, each containing the antifungal agent, miconazole nitrate, USP 1-[2,4-Dichloro-β-[(2,4- dichlorobenzyl)oxy] phenethyl]-imidazole mononitrate, 200 mg, in a hydrogenated vegetable oil base. The molecular formula is C18H14Cl4N2O•HNO3; the molecular weight is 479.14 and the structural formula may be represented as follows:

CLINICAL PHARMACOLOGY

Miconazole nitrate exhibits fungicidal activity in vitro against species of the genus Candida. The pharmacologic mode of action is unknown. Following intravaginal administration of miconazole nitrate, small amounts are absorbed. Administration of a single dose of miconazole nitrate vaginal suppositories (100 mg) to healthy subjects resulted in total recovery from the urine and feces of 0.85% (±0.43%) of the administered dose.

Animal studies indicate that the drug crossed the placenta and doses above those used in humans result in embryo and fetotoxicity (80 mg/kg, orally), although this has not been reported in human subjects (See PRECAUTIONS).

In multi-center clinical trials in 440 women with vulvovaginal candidiasis, the efficacy of treatment with the Miconazole Nitrate Vaginal Suppositories USP, 200 mg for 3 days was compared with treatment for 7 days with Miconazole Nitrate Vaginal Cream 2%. The clinical cure rates (free of microbiological evidence and clinical signs and symptoms of candidiasis at 8 to 10 days and 30 to 35 days post therapy) were numerically lower, although not statistically different, with the 3-Day Suppository when compared with the 7-Day Cream.

INDICATIONS AND USAGE

Miconazole Nitrate Vaginal Suppositories USP, 200 mg are indicated for the local treatment of vulvovaginal candidiasis (moniliasis). Effectiveness in pregnancy has not been established. As miconazole nitrate is effective only for candidal vulvovaginitis, the diagnosis should be confirmed by KOH smear and/or cultures. Other pathogens commonly associated with vulvovaginitis (Trichomonas and Haemophilus vaginalis [Gardnerella]) should be ruled out by appropriate laboratory methods.

CONTRAINDICATIONS

Patients known to be hypersensitive to this drug.

PRECAUTIONS

General

Discontinue drug if sensitization or irritation is reported during use. The base contained in the suppository formulation may interact with certain latex products, such as that used in vaginal contraceptive diaphragms. Concurrent use is not recommended. Miconazole Nitrate Vaginal Cream USP, 2% may be considered for use under these conditions.

Laboratory Tests

If there is a lack of response to Miconazole Nitrate Vaginal Suppositories, appropriate microbiological studies (standard KOH smear and/or cultures) should be repeated to confirm the diagnosis and rule out other pathogens.

Carcinogenesis, Mutagenesis, Impairment of Fertility

Long-term animal studies to determine carcinogenic potential have not been performed.

Fertility (Reproduction): Oral administration of miconazole nitrate in rats has been reported to produce prolonged gestation. However, this effect was not observed in oral rabbit studies. In addition, signs of fetal and embryo toxicity were reported in rat and rabbit studies, and dystocia was reported in rat studies after oral doses at and above 80 mg per kg. Intravaginal administration did not produce these effects in rats.

Pregnancy

Since imidazoles are absorbed in small amounts from the human vagina, they should not be used in the first trimester of pregnancy unless the physician considers it essential to the welfare of the patient.

Clinical studies, during which miconazole nitrate vaginal cream and suppositories were used for up to 14 days, were reported to include 541 pregnant patients. Follow-up reports available in 471 of these patients reveal no adverse effects or complications attributable to miconazole nitrate therapy in infants born to these women.

Nursing Mothers

It is not known whether miconazole is excreted in human milk. Because many drugs are excreted in human milk, caution should be exercised when miconazole nitrate is administered to a nursing woman.

ADVERSE REACTIONS

During clinical studies with Miconazole Nitrate Vaginal Suppositories USP, 200 mg, 301 patients were treated. The incidence of vulvovaginal burning, itching or irritation was 2%. Complaints of cramping (2%) and headaches (1.3%) were also reported. Other complaints (hives, skin rash) occurred with less than a 0.5% incidence. The therapy-related dropout rate was 0.3%.

To report SUSPECTED ADVERSE EVENTS, contact Teva Pharmaceuticals USA, Inc., at 1-888-838-2872 or FDA at 1-800-FDA-1088 or http://www.fda.gov/ for voluntary reporting of adverse reactions.

OVERDOSAGE

Overdosage of miconazole nitrate in humans has not been reported to date. In mice, rats, guinea pigs and dogs, the oral LD50 values were found to be 578.1, greater than 640, 275.9 and greater than 160 mg/kg, respectively.

DOSAGE AND ADMINISTRATION

Miconazole Nitrate Vaginal Suppositories USP, 200 mg: One suppository (miconazole nitrate, 200 mg) is inserted intravaginally once daily at bedtime for three consecutive days. Before prescribing another course of therapy, the diagnosis should be reconfirmed by smears and/or cultures to rule out other pathogens.

HOW SUPPLIED

Miconazole Nitrate Vaginal Suppositories USP, 200 mg are available as elliptically shaped white to off-white suppositories in packages of three with a vaginal applicator NDC 0472-1738-03.

Store at controlled room temperature 15° to 30°C (59° to 86°F).

Manufactured for:
Teva Pharmaceuticals USA, Inc.
Parsippany, NJ 07054

Rev. A 7/2020

PATIENT’S INSTRUCTIONS

Miconazole Nitrate (mye konꞌ a zole nyeꞌ trate)
Vaginal Suppositories USP, 200 mg

3-DAY THERAPY

Three oval suppositories, for use inside the vagina only.
Designed to be inserted into the vagina.

HOW TO USE:

Place one suppository into the vagina each night at bedtime for 3 nights, as directed by your doctor. The miconazole nitrate vaginal suppository is self-lubricating and may be inserted with or without the applicator
A. Insertion with the applicator

1. Filling the applicator:
Tear off one suppository from the strip. Separate the plastic wrap at the pointed end with your thumb. With thumb and forefinger of each hand, hold the plastic tabs and pull apart. Gently remove the suppository from the plastic wrap.

Place the flat end of the suppository into the open end of the applicator as shown. You are now ready to insert the suppository into the vagina.

2. Using the applicator:
Lie on your back with your knees drawn up toward your chest.

Holding the applicator by the ribbed end of the barrel, gently insert it into the vagina as far as it will comfortably go. Press the plunger to release the suppository into the vagina.

Remove the applicator from the vagina.

3. Cleaning the applicator:
After each use, you should thoroughly clean the applicator by the following procedure:

Pull the plunger out of the barrel. Wash both pieces with lukewarm, soapy water, and dry them thoroughly. Put the applicator back together by gently pushing the plunger into the barrel as far as it will go.

B. Insertion without the applicator

Lie on your back with your knees drawn up toward your chest. Place the suppository on the tip of your finger as shown. Insert the suppository gently into the vagina as far as it will comfortably go.

NOTE: Store at controlled room temperature 15° to 30°C (59° to 86°F).
See end flap for lot number and expiration date.

A WORD ABOUT YEAST INFECTIONS

Why do yeast infections occur?

Yeast infections are caused by an organism called Candida (KAN di duh). It may be present in small and harmless amounts in the mouth, digestive track, and vagina. Sometimes the natural balance of the vagina becomes upset. This may lead to rapid growth of Candida, which results in a yeast infection. Symptoms of yeast infection include itching, burning, redness, and an abnormal discharge. Your doctor can make the diagnosis of a yeast infection by evaluating your symptoms and looking at a sample of the discharge under the microscope.

How can I prevent yeast infections?

Certain factors may increase your chance of developing a yeast infection. These factors don’t actually cause the problem, but they may create a situation that allows the yeast to grow rapidly.

Clothing: Tight jeans, nylon underwear, pantyhose, and wet bathing suits can hold in heat and moisture (two conditions in which yeast organisms thrive). Looser pants or skirts, 100% cotton underwear, and stockings may help avoid this problem.

Diet: Cutting down on sweets, milk products, and artificial sweeteners reduce the risk of yeast infections.

Antibiotics: Antibiotics work by eliminating disease-causing organisms. While they are helpful in curing other problems, antibiotics may lead to an overgrowth of Candida in the vagina.

Pregnancy: Hormonal changes in the body during pregnancy encourage the growth of yeast. This is a very common time for an infection to occur. Until the baby is born, it may be hard to completely eliminate yeast infections. If you believe you are pregnant, tell your doctor.

Menstruation: Sometimes, monthly changes in hormone levels may lead to yeast infections.

Diabetes: In addition to heat and moisture, yeast thrives on sugar. Because diabetics often have sugar in their urine, their vaginas are rich in this substance. Careful control of diabetes may help prevent yeast infection.

Controlling these factors can help eliminate yeast infections and may prevent them from coming back.

Some other helpful tips:

1. For best results, be sure to use the medication as prescribed by your doctor, even if you feel better very quickly.
2. Avoid sexual intercourse, if your doctor advises you to do so. The suppository formulation (not the cream) may damage the diaphragm. Therefore, use of the diaphragm during therapy with the suppository is not recommended. Consult your physician.
3. If your partner has any penile itching, redness, or discomfort, he should consult his physician and mention that you are being treated for a yeast infection.
4. You can use the medication even if you are having your menstrual period. However, you should not use tampons because they may absorb the medication. Instead, use external sanitary pads or napkins until you have finished your medication or if the vaginal medication leaks.
5. Dry the genital area thoroughly after showering, bathing, or swimming. Change out of a wet bathing suit or damp exercise clothes as soon as possible. A dry environment is less likely to encourage the growth of yeast.
6. Wipe from front to rear (away from the vagina) after a bowel movement.
7. Don’t douche unless your doctor specifically tells you to do so. Douching may disturb the vaginal balance.
8. Don’t scratch if you can help it. Scratching can cause more irritation and spread the infection.
9. Discuss with your physician any medication you are already taking. Certain types of medication can make your vagina more susceptible to infection.
10. Eat nutritious meals to promote your general health.

IF YOU HAVE A QUESTION
Contact Teva Pharmaceuticals USA, Inc. at 1-888-838-2872 or call your doctor for medical advice about side effects. You may report side effects to FDA at 1-800-FDA-1088.

Manufactured for:
Teva Pharmaceuticals USA, Inc.
Parsippany, NJ 07054

Rev. A 7/2020

PACKAGE LABEL.PRINCIPAL DISPLAY PANEL

NDC 0472-1738-03

Miconazole Nitrate Vaginal Suppositories USP, 200 mg

For Vaginal Yeast Infections
3-Day Regimen

Rx only

3 vaginal suppositories with applicator